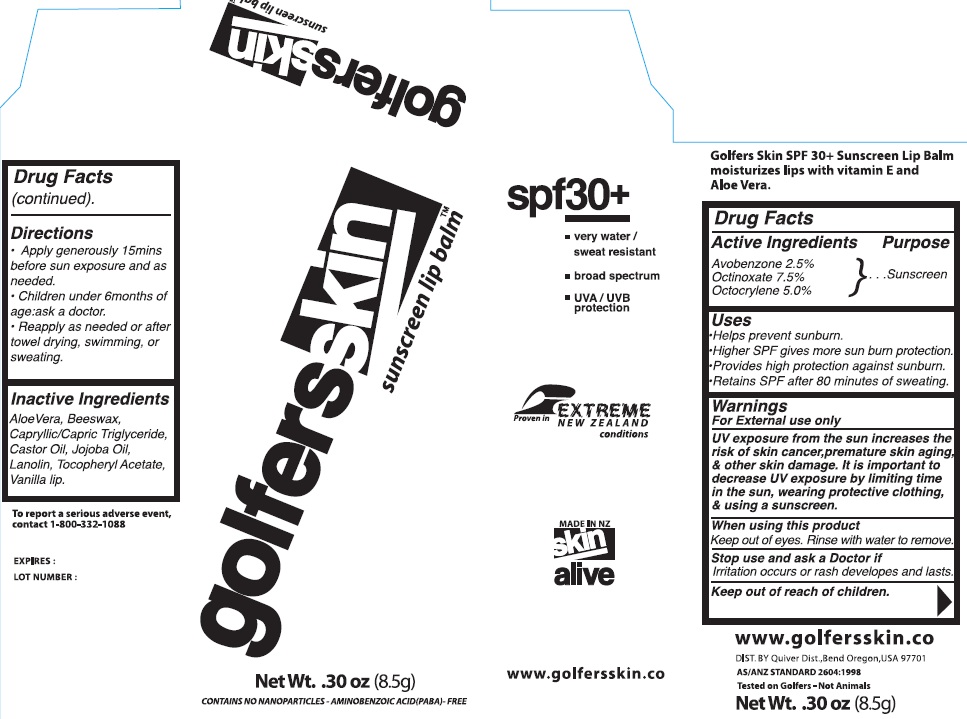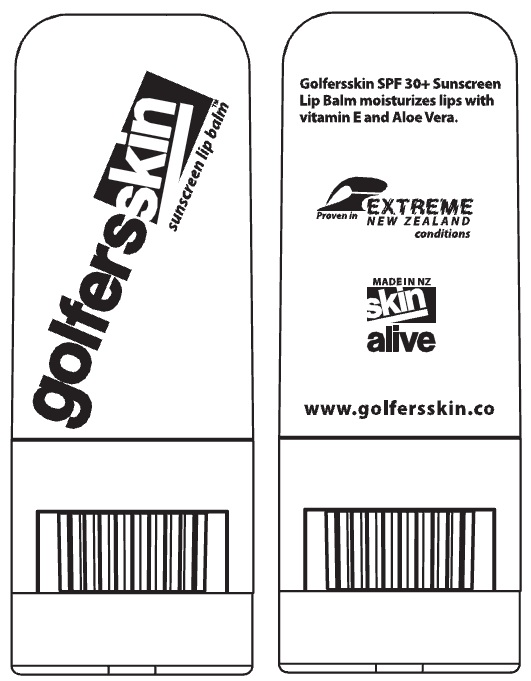 DRUG LABEL: GolfersSkin Sunscreen Lip Balm
NDC: 75916-0664 | Form: STICK
Manufacturer: Skin Alive, Ltd.
Category: otc | Type: HUMAN OTC DRUG LABEL
Date: 20110119

ACTIVE INGREDIENTS: AVOBENZONE 2.5 g/100 g; OCTINOXATE 7.5 g/100 g; OCTOCRYLENE 5 g/100 g
INACTIVE INGREDIENTS: ALOE VERA LEAF; YELLOW WAX; MEDIUM-CHAIN TRIGLYCERIDES; JOJOBA OIL; LANOLIN; .ALPHA.-TOCOPHEROL ACETATE, DL-; VANILLA

Golfers Skin Sunscreen Lip Balm

Active Ingredients

Avobenzone 2.5%
Octinoxate 7.5%
Octocrylene 5.0%

Purpose

Sunscreen

Uses

Helps prevent sunburn

Higher SPF gives more sunburn protection

Provides high protection against sunburn

Retains SPF after 80 minutes of sweating.

Warnings

For external use only

UV exposure from the sun increases the risk of skin cancer, premature skin aging and other skin damage. It is important to decrease UV exposure by limiting time in the sun, wearing protective clothing and using a sunscreen.

When using this product

Keep out of eyes. Rinse with water to remove.

Stop use and ask a doctor

if irritation occurs or rash develops and lasts.

Keep out of reach of children.

Directions
Apply generously 15 mins before sun exposure and as needed
Children under 6 months of age; ask a doctor
Reapply as needed or after towel drying, swimming or sweating.

Inactive Ingredients

Aloe vera, Beeswax, Capryllic/Capric Triglyceride, Castor Oil, Jojoba Oil, Lanolin, Tocopheryl Acetate, Vanilla lip

DESCRIPTION

Golfers Skin SPF 30+ Sunscreen Lip Balm moisturizes lips with Vitamin E and Aloe Vera

To report a serious adverse event, contact 1-800-332-1088

Expires:

Lot Number:

www.golfersskin.co

DIST. BY Quiver Dist, Bend Oregon, USA 97701

AS/ANZ STANDARD 2604-1998

Tested on Golfers - Not Animals

Net Wt. .3oz (8.5g)

PACKAGE LABEL

SPF 30+

very water / sweat resistant

broad spectrum

UVA/UVB protection

Proven in extreme New Zealand conditions

Golfers Skin sunscreen lip balm

Net Wt. .30 oz (8.5g)

contains no nanoparticles - aminobenzoic acid (PABA)-free